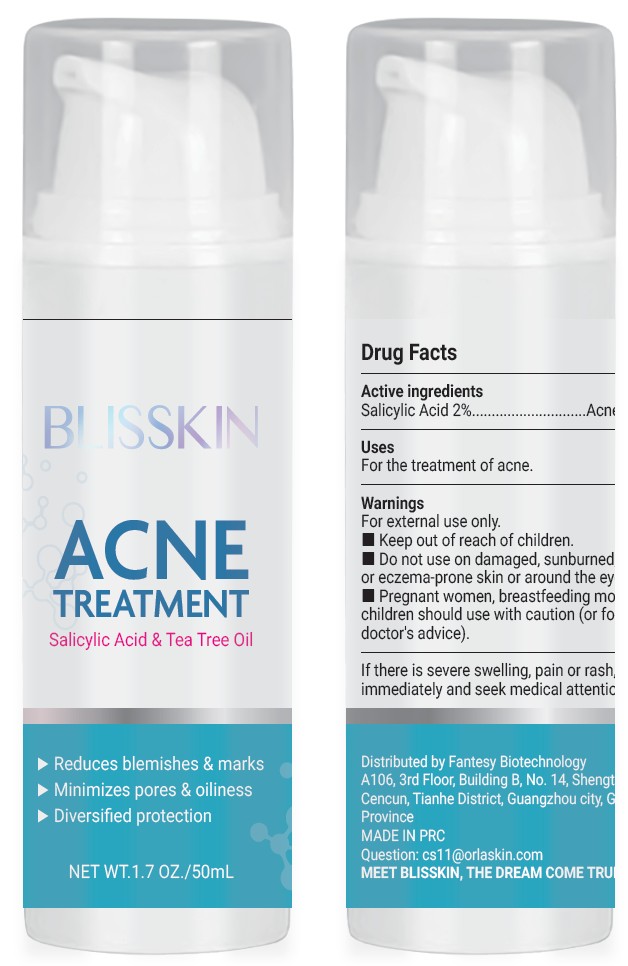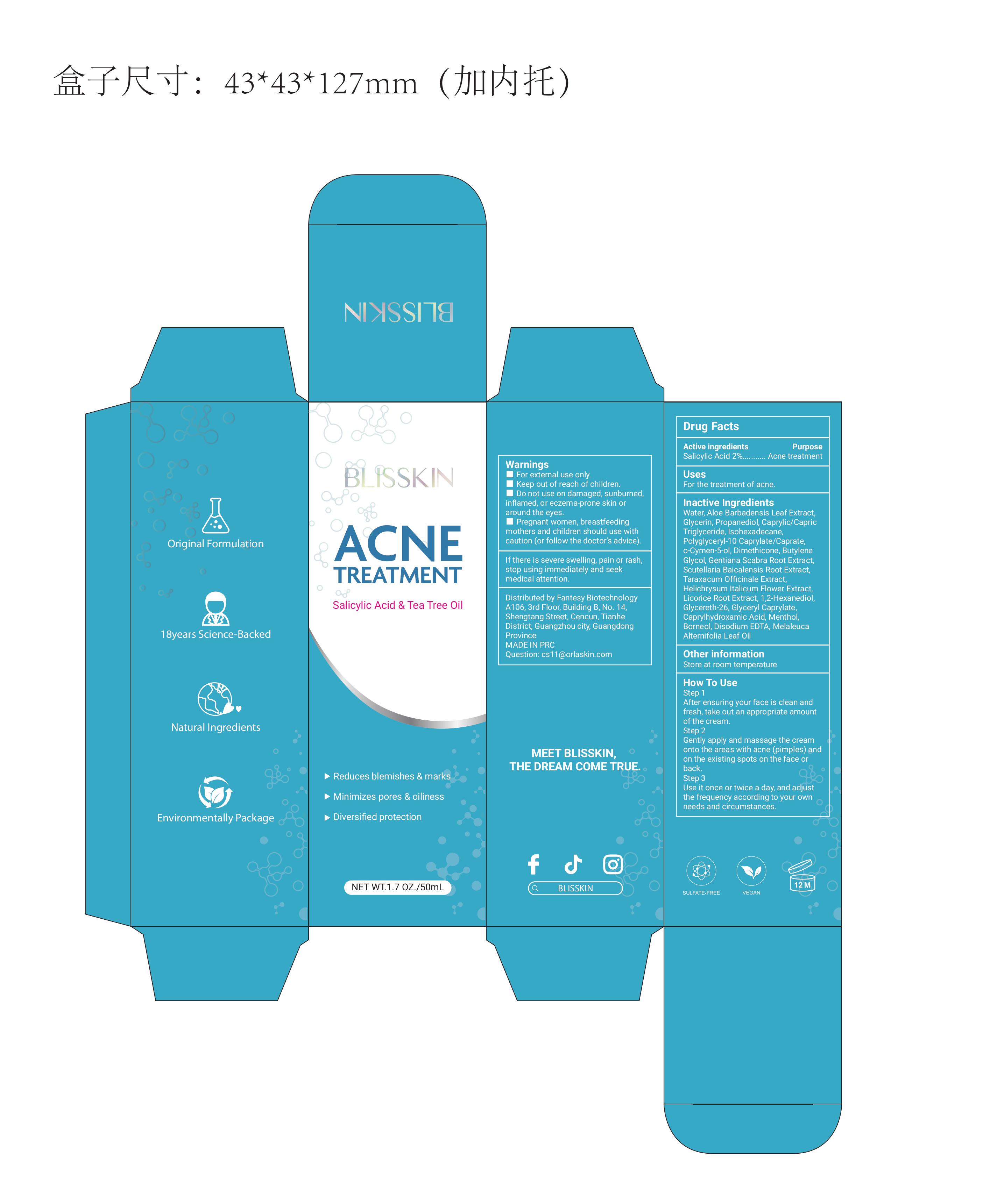 DRUG LABEL: Acne Treatment Cream
NDC: 84356-006 | Form: CREAM
Manufacturer: Guangzhou Yapeng Refinement Chemical Co., Ltd.
Category: otc | Type: HUMAN OTC DRUG LABEL
Date: 20250620

ACTIVE INGREDIENTS: SALICYLIC ACID 2 g/100 mL
INACTIVE INGREDIENTS: ALOE BARBADENSIS LEAF; GLYCERIN; PROPANEDIOL; BUTYLENE GLYCOL; TARAXACUM OFFICINALE; GLYCERETH-26; GLYCERYL CAPRYLATE; CAPRYLIC/CAPRIC TRIGLYCERIDE; WATER; DISODIUM EDTA-COPPER; POLYGLYCERYL-10 CAPRYLATE; MELALEUCA ALTERNIFOLIA LEAF; MENTHOL; GLYCYRRHIZA GLABRA (LICORICE) RHIZOME/ROOT; ISOHEXADECANE; CAPRYLHYDROXAMIC ACID; BORNEOL; O-CYMEN-5-OL; DIMETHICONE; GENTIANA SCABRA ROOT; SODIUM HYALURONATE; SCUTELLARIA BAICALENSIS ROOT; HELICHRYSUM ITALICUM FLOWER; 1,2-HEXANEDIOL

ACTIVE INGREDIENT

Salicylic Acid

INDICATIONS AND USAGE

For the treatment of acne.

DO NOT USE

For external use only.Keep out of reach of children.

Do not use on damaged, sunburned, inflamed,or eczema-prone skin or around the eyes.

Pregnant women, breastfeeding mothers and children should use with caution (or follow the

doctor's advice).

STOP USE

If there is severe swelling, pain or rash, stop using

immediately and seek medical attention

Keep out of reach of children.The above warning information has been listed on the label

WARNINGS

For external use only.
Keep out of reach of children.
Do not use on damaged, sunburned, inflamed,or eczema-prone skin or around the eyes.
Pregnant women, breastfeeding mothers and children should use with caution (or follow the doctor's advice).

INACTIVE INGREDIENT

Water, Aloe Barbadensis Leaf Extract,Glycerin, Propanediol, Caprylic/CapricTriglyceride, lsohexadecane.Polyglycery1-10 Caprylate/Caprate,o-Cymen-5-ol, Dimethicone, ButyleneGlycol, Gentiana Scabra Root ExtractScutellaria Baicalensis Root Extract,Taraxacum Officinale Extract,Helichrysum ltalicum Flower Extract,Licorice Root Extract, 1,2-HexanediolGlycereth-26, Glyceryl Caprylate,Caprylhydroxamic Acid, Menthol,Borneol, Disodium EDTA, MelaleucaAlternifolia Leaf Oil

PURPOSE

Acne treatment
Reduces blemishes & marks
Minimizes pores & oiliness
Diversified protection

DOSAGE AND ADMINISTRATION

Use it once or twice a day, and adjustthe frequency according to your ownneeas and circumstances